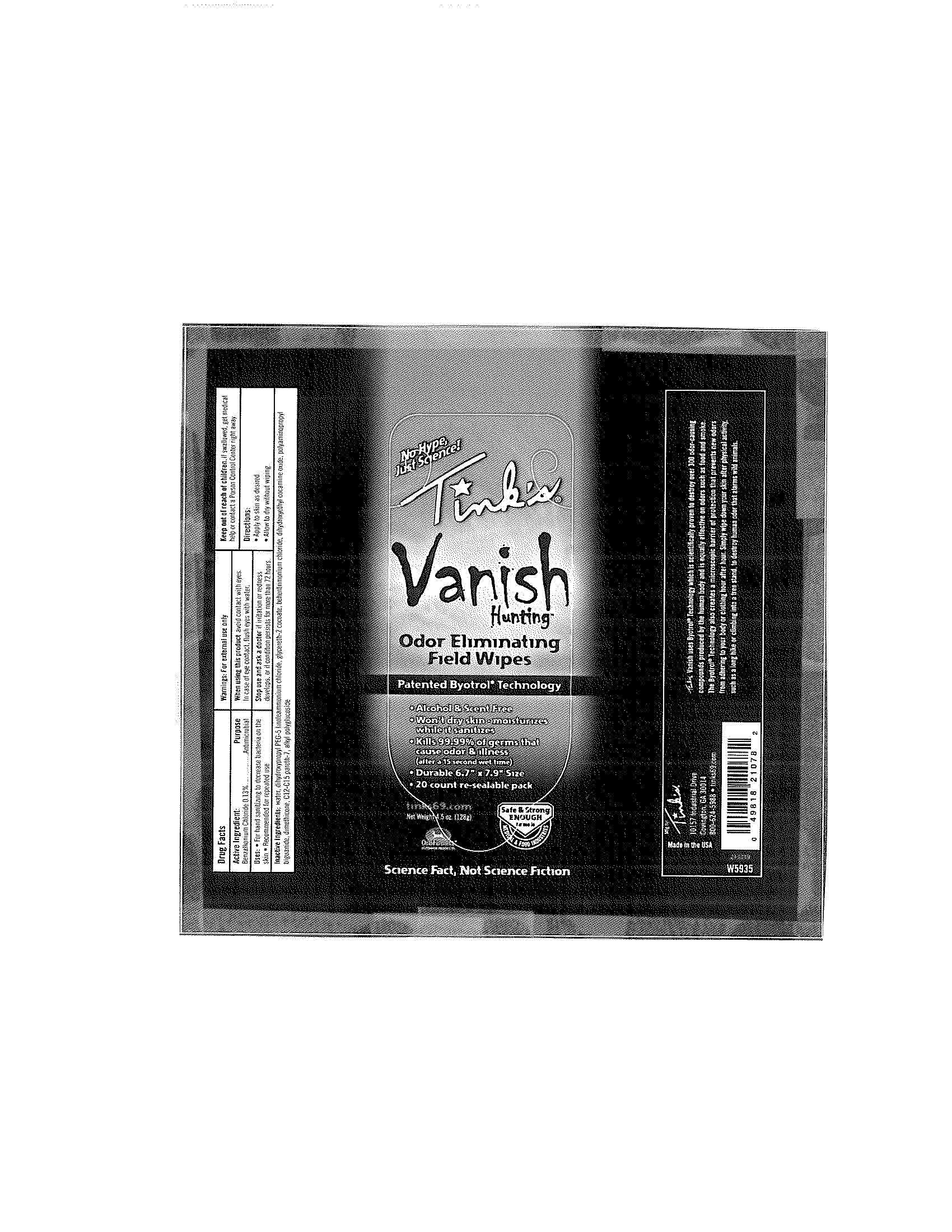 DRUG LABEL: Vanish
NDC: 52473-001 | Form: LIQUID
Manufacturer: Tinks
Category: otc | Type: HUMAN OTC DRUG LABEL
Date: 20100707

ACTIVE INGREDIENTS: Benzalkonium Chloride 0.13 mL/100 mL
INACTIVE INGREDIENTS: Water; Dihydroxypropyl PEG-5 linoleammonium chloride; Glycereth-2 cocoate; Behentrimonium chloride; Dihydroxyethyl cocamine oxide; Polyaminopropyl biguanide; Dimethicone

Drug Facts

Active Ingredient

Benzalkonium Chloride 0.13%

Purpose

Antimicrobial

Uses

For hand sanitizing to decrease bacteria on the skin

Recommended for repeated use

Warnings

For external use only

When using this product avoid contact with eyes.

In case of eye contact, flush eyes with water.

Stop use and ask a doctor if irritation or redness develops, or if conditions persists for more than 72 hours.

Keep out of reach of children. If swallowed, get medical help or contact a Poison Control Center right away.

Directions

Apply to skin as desired.

Allow to dry without wiping.

Inactive Ingredients

water, dihydroxypropyl PEG-5 linoleammonium chloride, glycereth-2 cocoate, behentrimonium chloride, dihydroxyethyl cocamine oxide, polyaminopropyl biguanide, dimethicone, C12-15 pareth-7, alkyl polyglucoside

PACKAGE LABEL

No Hype
Just Science
Tinks
Vanish
Hunting
Odor Eliminating Field Wipes
Patented Byotrol Technology
Alcohol and Scent Free
Wont dry skin - moisturizes while it sanitizes
Kills 99.99% of germs that cause odor and illness
(after a 15 second wet time)
Durable 6.7" by 7.9" Size
20 count re-sealable pack
tinks69.com
Net Weight: 4.5 oz (128g)
Safe and Strong enough for use in Medical and Food Industries
Science Fact, Not Science Fiction